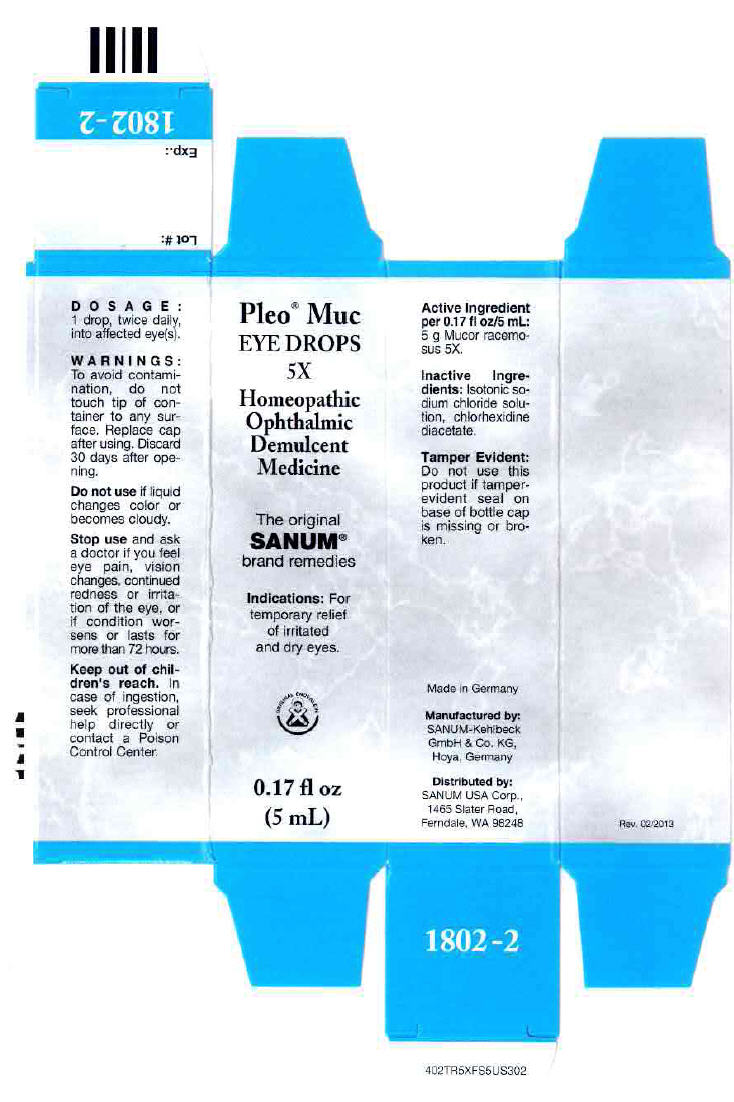 DRUG LABEL: Pleo Muc
NDC: 60681-1802 | Form: SOLUTION/ DROPS
Manufacturer: Sanum Kehlbeck GmbH & Co. KG
Category: homeopathic | Type: HUMAN OTC DRUG LABEL
Date: 20130820

ACTIVE INGREDIENTS: mucor racemosus 5 [hp_X]/5 mL
INACTIVE INGREDIENTS: sodium chloride; Water

Pleo® Muc EYE DROPS 5X

PURPOSE

Homeopathic Ophthalmic Demulcent Medicine

Indications

For temporary relief of irritated and dry eyes.

Active Ingredient per 0.17 fl oz/5 mL

5 g Mucor racemosus 5X.

Inactive Ingredients

Isotonic sodium chloride solution, chlorhexidine diacetate.

Tamper Evident

Do not use this product if tamper-evident seal on base of bottle cap is missing or broken.

DOSAGE

1 drop, twice daily, into affected eye(s).

WARNINGS

To avoid contamination, do not touch tip of container to any surface. Replace cap after using. Discard 30 days after opening.

Do not use if liquid changes color or becomes cloudy.

Stop use and ask a doctor if you feel eye pain, vision changes, continued redness or irritation of the eye, or if condition worsens or lasts for more than 72 hours.

KEEP OUT OF REACH OF CHILDREN

Keep out of children's reach. In case of ingestion, seek professional help directly or contact a Poison Control Center.

Manufactured by:
SANUM-Kehlbeck
GmbH & Co. KG,
Hoya, Germany

Distributed by:
SANUM USA Corp.,
1465 Slater Road,
Ferndale, WA 98248

PRINCIPAL DISPLAY PANEL - 5 mL Bottle Carton

Pleo® Muc
EYE DROPS
5X

Homeopathic
Ophthalmic
Demulcent
Medicine

The original
SANUM®
brand remedies

Indications: For
temporary relief
of irritated
and dry eyes.

ORIGINAL ENDERLEIN

0.17 fl oz
(5 mL)